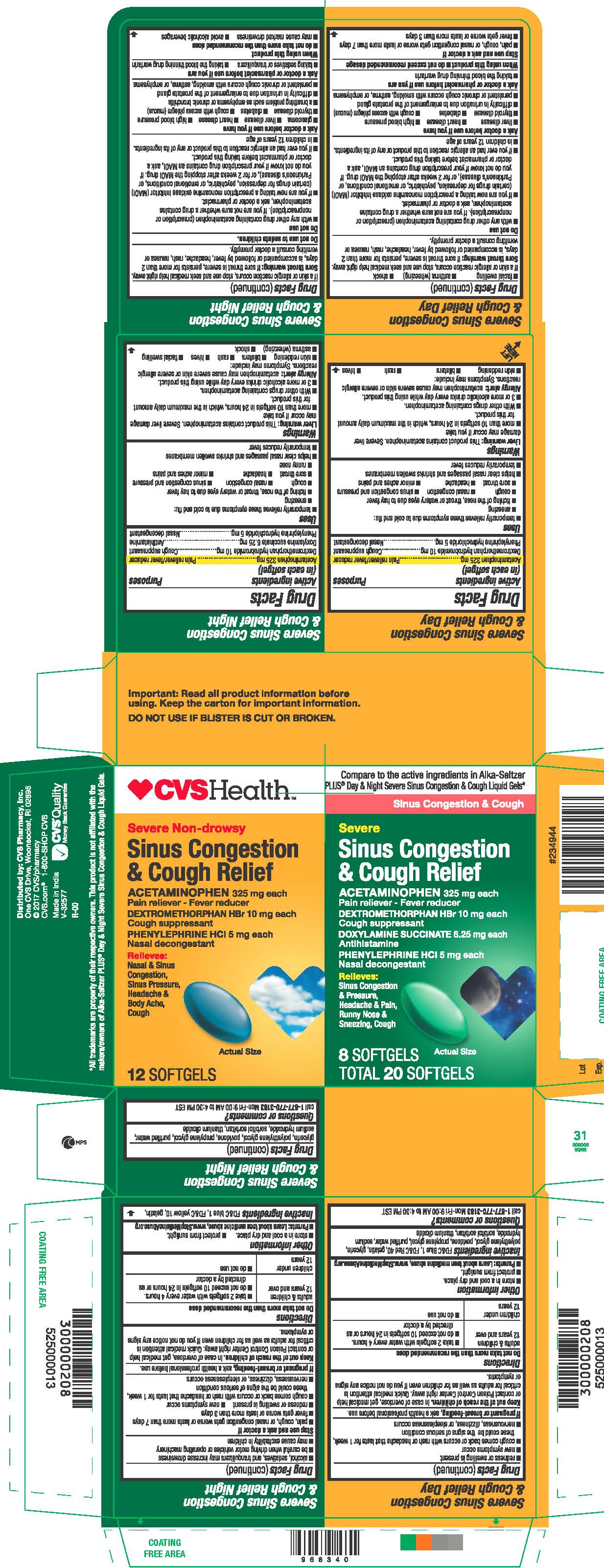 DRUG LABEL: Acetaminophen Dextromethorphan HBr Doxylamine succinate Phenylephrine HCl
NDC: 69842-305 | Form: CAPSULE, LIQUID FILLED
Manufacturer: CVS PHARMACY,INC
Category: otc | Type: HUMAN OTC DRUG LABEL
Date: 20170719

ACTIVE INGREDIENTS: DEXTROMETHORPHAN HYDROBROMIDE 10 mg/1 1; ACETAMINOPHEN 325 mg/1 1; DOXYLAMINE SUCCINATE 6.25 mg/1 1; PHENYLEPHRINE HYDROCHLORIDE 5 mg/1 1
INACTIVE INGREDIENTS: FD&C BLUE NO. 1; GELATIN; GLYCERIN; POLYETHYLENE GLYCOLS; POVIDONE; PROPYLENE GLYCOL; FD&C RED NO. 40; WATER; SODIUM HYDROXIDE; SORBITAN; TITANIUM DIOXIDE

Severe Non-Drowsy
Sinus Congestion and Cough Relief
Acetaminophen 325 mg each
Dextromethorphan hydrobromide 10 mg each
Phenylephrine hydrochloride 5 mg each
Severe
Sinus Congestion and Cough Relief
Acetaminophen 325 mg each
Dextromethorphan hydrobromide 10 mg each
Doxylamine succinate 6.25 mg each
Phenylephrine hydrochloride 5 mg each

Active ingredients

Severe Sinus Congestion & Cough Relief Day

(in each Softgel)

Acetaminophen | 325 mg
Dextromethorphan hydrobromide | 10 mg
Phenylephrine hydrochloride | 5 mg

Purposes

Pain reliever/fever reducer
Cough suppressant
Nasal decongestant

Uses

temporarily relieves these symptoms due to cold and flu:

- sneezing
- itching of the nose, throat or watery eyes due to hay fever
- cough
- nasal congestion
- sinus congestion and pressure
- sore throat
- head ache
- minor aches and pains

helps clear nasal passages and shrinks swollen membranes

temporarily reduces fever

Liver warning

This product contains acetaminophen. Severe liver damage may occur if you take
• more than 10 softgels in 24 hours, which is the maximum daily amount for this product
• with other drugs containing acetaminophen
• 3 or more alcoholic drinks every day while using this product

Allergy alert

acetaminophen may cause severe skin or severe allergic reactions. Symptoms may include:
• skin reddening

• blisters
• rash
• hives
• facial swelling
• asthma (wheezing)
• shock
If a skin or allergic reaction occurs, stop use and seek medical help right away.

Sore throat warning

If sore throat is severe, persists for more than 2 days, is accompanied or followed by fever, headache, rash, nausea or vomiting consult a doctor promptly.

Do not use

• with any other drug containing acetaminophen (prescription or nonprescription). If you are not sure whether a drug contains acetaminophen, ask a doctor or pharmacist.
• if you are now taking a prescription monoamine oxidase inhibitor (MAOI) (certain drugs for depression, psychiatric, or emotional conditions, or Parkinson’s disease), or for 2 weeks after stopping the MAOI drug. If you do not know if your prescription drug contains an MAOI, ask a doctor or pharmacist before taking this product.
• if you ever had an allergic reaction to this product or any of its ingredients.
• in children 12 years of age.

Ask a doctor before use if you have

• liver disease
• heart disease
• high blood pressure
• thyroid disease
• diabetes
• cough with excess phlegm (mucus)
• difficulty in urination due to enlargement of the prostate gland
• persistent or chronic cough occurs with smoking, asthma, or emphysema

Ask a doctor or pharmacist before use if you are

taking the blood thinning drug warfarin

When using this product

do not exceed recommended dosage

Stop use and ask a doctor if

• pain, cough, or nasal congestion gets worse or lasts more than 7 days
• fever gets worse or lasts more than 3 days
• redness or swelling is present
• new symptoms occur
• cough comes back or occurs with rash or head ache that lasts for 1 week, these could be the signs of serious condition
• nervousness, dizziness, or sleeplessness occurs

If pregnant or breast-feeding

ask a health professional before use.

Keep out of the reach of children

In case of overdose, get medical help or contact Poison Control Center right away. Quick medical attention is critical for adults as well as for children even if you do not notice any signs or symptoms.

Directions

Do not take more than the recommended dose
adults & children under 12 years and over
- take 2 softgels with water every 4 hours.
- do not exceed 10 softgels in 24 hours or as directed by a doctor
children under 12 years
- do not use

Other information

• store in a cool and dry place.
• protect from sunlight.
• Parents: Learn about teen medicine abuse, WWW.StopMedicineAbuse.org

Inactive ingredients

FD&C Blue 1, FD&C Red 40, gelatin, glycerin, polyethylene glycol, povidone, propylene glycol, purified water, sodium hydroxide, sorbitol sorbitan, titanium dioxide

Questions or comments?

call 1-877-770-3183 Mon-Fri 9:00 AM to 4:30 PM EST

Active ingredients

Severe Sinus Congestion & Cough Relief Night

(in each Softgel)

Acetaminophen | 325 mg
Dextromethorphan hydrobromide | 10 mg
Doxylamine succinate | 6.25 mg
Phenylephrine hydrochloride | 5 mg

Purposes

Pain reliever/fever reducer
Cough suppressant
Antihistamine
Nasal decongestant

Uses

temporarily relieves these symptoms due to cold and flu:

- sneezing
- itching of the nose, throat or watery eyes due to hay fever
- cough
- nasal congestion
- sinus congestion and pressure
- sore throat
- headache
- minor aches and pains
- runny nose

helps clear nasal passages and shrinks swollen membranes
temporarily reduces fever

Liver warning

This product contains acetaminophen. Severe liver damage may occur if you take
• more than 10 softgels in 24 hours, which is the maximum daily amount for this product
• with other drugs containing acetaminophen
• 3 or more alcoholic drinks every day while using this product

Allergy alert

acetaminophen may cause severe skin or severe allergic reactions. Symptoms may include:
• skin reddening
• blisters
• rash
• hives
• facial swelling
• asthma (wheezing)
• shock
If a skin or allergic reaction occurs, stop use and seek medical help right away.

Sore throat warning

If sore throat is severe, persists for more than 2 days, is accompanied or followed by fever, headache, rash, nausea or vomiting consult a doctor promptly.

Warnings

Do not use to sedate children

Do not use

• with any other drug containing acetaminophen (prescription or nonprescription). If you are not sure whether a drug contains acetaminophen, ask a doctor or pharmacist.
• if you are now taking a prescription monoamine oxidase inhibitor (MAOI) (certain drugs for depression, psychiatric, or emotional conditions, or Parkinson’s disease), or for 2 weeks after stopping the MAOI drug. If you do not know if your prescription drug contains an MAOI, ask a doctor or pharmacist before taking this product.
• if you ever had an allergic reaction to this product or any of its ingredients.
• in children 12 years of age.

Ask a doctor before use if you have

• liver disease
• heart disease
• high blood pressure
• thyroid disease
• diabetes

• glaucoma

• cough with excess phlegm (mucus)
• a breathing problem such as emphysema or chronic bronchitis
• difficulty in urination due to enlargement of the prostate gland
• persistent or chronic cough occurs with smoking, asthma, or emphysema

Ask a doctor or pharmacist before use if you are

• taking sedatives or tranquilizers
• taking a blood thinning drug warfarin

When using this product

• do not exceed recommended dose
• may cause marked drowsiness
• avoid alcoholic beverages
• alcohol, sedatives, and tranquilizers may increase drowsiness
• be careful when driving motor vehicles or operating machinery
• may cause excitability in children

Stop use and ask a doctor if

• pain, cough, or nasal congestion gets worse or lasts more than 7 days
• fever gets worse or lasts more than 3 days
• redness or swelling is present
• new symptoms occur
• cough comes back or occurs with rash or head ache that lasts for 1 week, these could be the signs of serious condition
• nervousness, dizziness, or sleeplessness occurs

If pregnant or breast-feeding

ask a health professional before use.

Keep out of the reach of children

In case of overdose, get medical help or contact Poison Control Center right away. Quick medical attention is critical for adults as well as for children even if you do not notice any signs or symptoms

Directions

Do not take more than the recommended dose
adults & children under 12 years and over
- take 2 softgels with water every 4 hours.
- do not exceed 10 softgels in 24 hours or as directed by a doctor
children under 12 years
- do not use

Other information

• store in a cool and dry place.
• protect from sunlight.
• Parents: Learn about teen medicine abuse, WWW.StopMedicineAbuse.org

Inactive ingredients

FD&C blue 1, FD&C yellow 10, gelatin, glycerin, polyethylene glycol, povidone, propylene glycol, purified water, sodium hydroxide, sorbitol sorbitan, titanium dioxide.

Questions or comments?

call 1-877-770-3183 Mon-Fri 9:00 AM to 4:30 PM EST